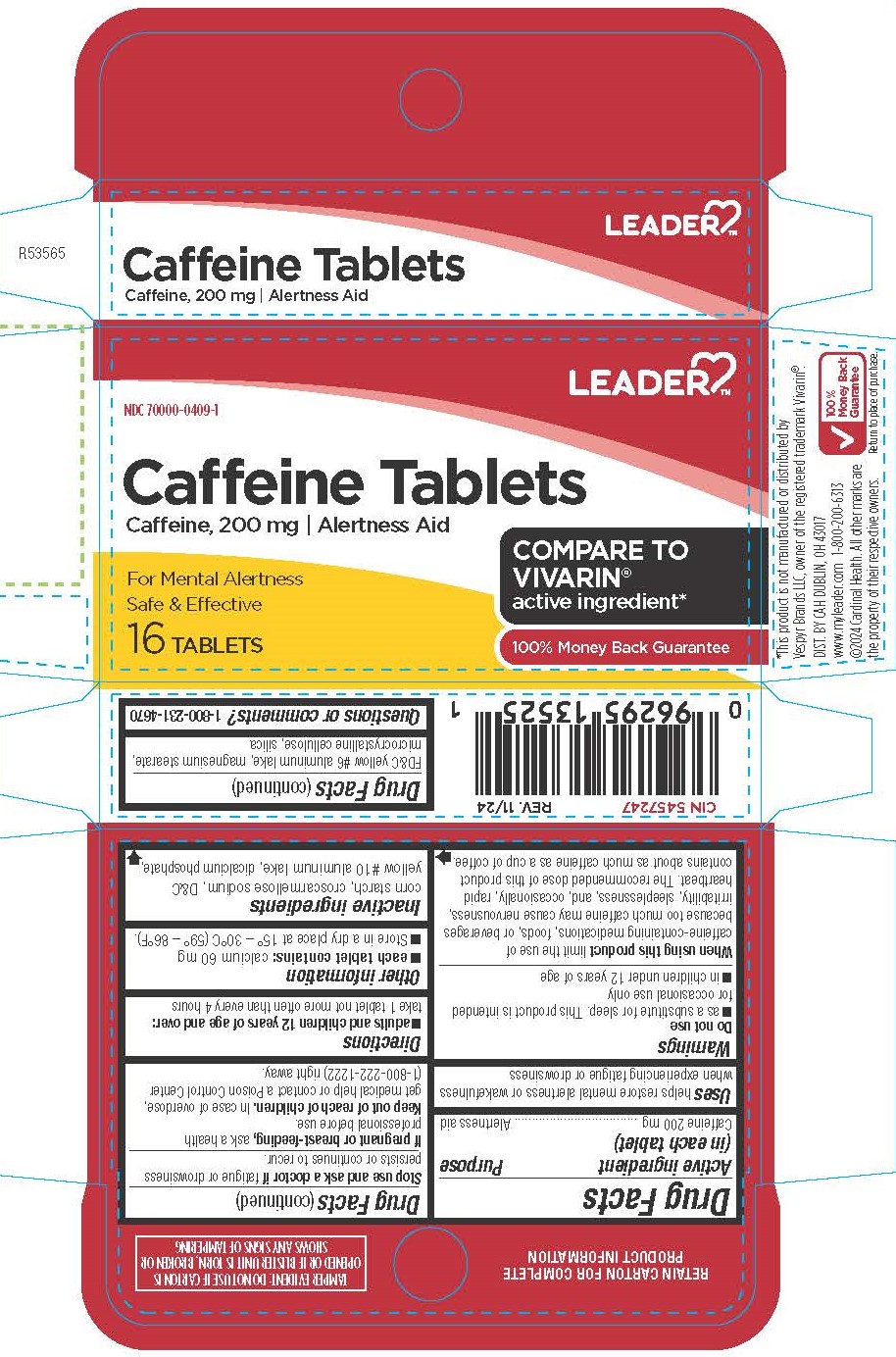 DRUG LABEL: Caffeine
NDC: 70000-0409 | Form: TABLET
Manufacturer: LEADER/ Cardinal Health 110, Inc.
Category: otc | Type: HUMAN OTC DRUG LABEL
Date: 20260128

ACTIVE INGREDIENTS: CAFFEINE 200 mg/1 1
INACTIVE INGREDIENTS: CROSCARMELLOSE SODIUM; DIBASIC CALCIUM PHOSPHATE DIHYDRATE; D&C YELLOW NO. 10; FD&C YELLOW NO. 6; MICROCRYSTALLINE CELLULOSE; STARCH, CORN; MAGNESIUM STEARATE; SILICON DIOXIDE

5009-Cardinal

Drug Facts

Active ingredient (in each tablet)

Caffeine 200 mg

Purpose

Alertness aid

Uses

helps restore mental alertness or wakefulness when experiencing fatigue or drowsiness

Warnings

Do not use

■as a substitute for sleep. This product is intended for occasional use only

■in children under 12 years of age

When using this product limit the use of caffeine-containing medications, foods, or beverages because too much caffeine may cause nervousness, irritability, sleeplessness, and, occasionally, rapid heartbeat. The recommended dose of this product contains about as much caffeine as a cup of coffee.

Stop use and ask a doctor if fatigue or drowsiness persists or continues to recur.

PREGNANCY OR BREAST FEEDING

If pregnant or breast-feeding, ask a health professional before use.

Keep out of reach of children.

OVERDOSAGE

In case of overdose, get medical help or contact a Poison Control Center (1-800-222-1222) right away.

Directions

■ adults and children 12 years of age and over: take 1 tablet not more often than every 4 hours

Other information

■ each tablet contains: calcium 60 mg

■ Store in a dry place at 15°-30°C (59°-86°F).

Inactive ingredients

corn starch, croscarmellose sodium, D&C yellow #10 aluminum lake, dicalcium phosphate, FD&C yellow #6 aluminum lake, magnesium stearate, microcrystalline cellulose, silica

Questions or comments?

1-800-231-4670

RETAIN CARTON FOR COMPLETE PRODUCT INFORMATION

TAMPER EVIDENT: DO NOT USE IF CARTON IS OPENED OR IF BLISTER UNIT IS TORN, BROKEN OR SHOWS ANY SIGNS OF TAMPERING

*This product is not manufactured or distributed by Vespyr Brands LLC, owner of the registered trademark Vivarin®.

DIST. BY CAH, DUBLIN, OH 43017

www.myleader.com 1-800-200-6313

©2024 Cardinal Health. All other marks are the property of their respective owners.

100% Money Back Guarantee

Return to place of purchase.

PACKAGE LABEL

Leader

NDC 70000-0409-1

Caffeine Tablets

Caffeine, 200mg/ Alertness Aid

For Mental Alertness

Safe & Effective

COMPARE TO VIVARIN® active ingredient*

100% Money Back Guarantee

16 Tablets